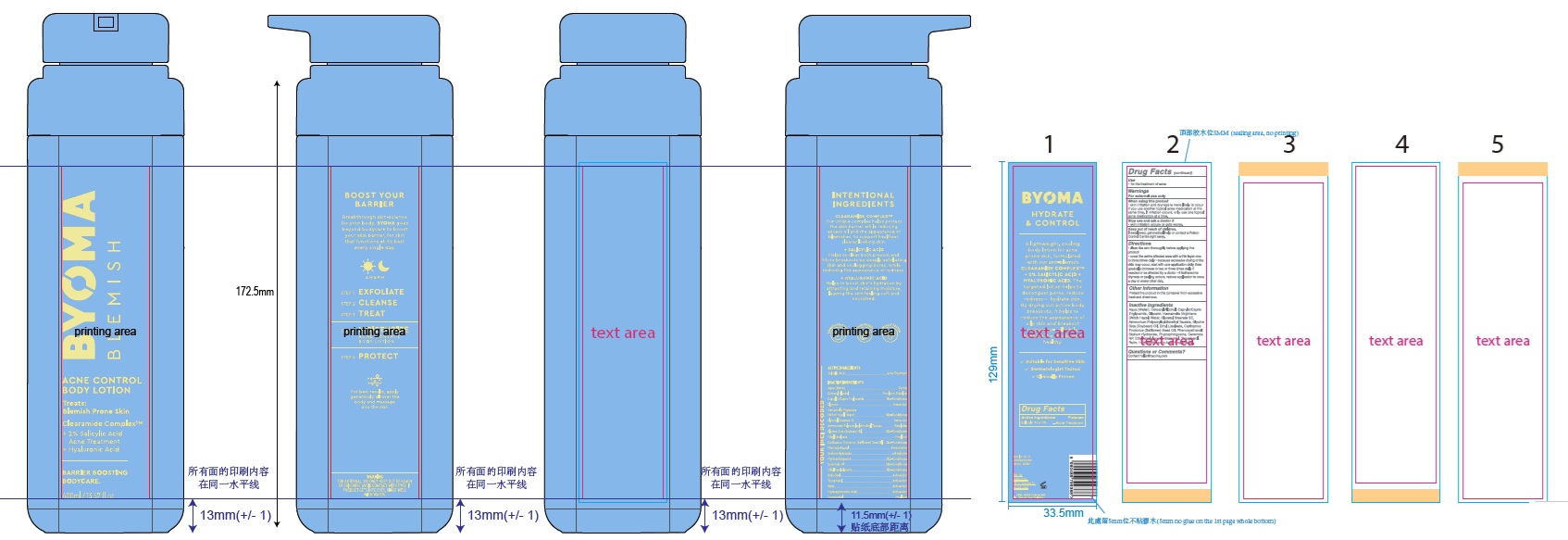 DRUG LABEL: Byoma Acne Control Body
NDC: 84821-004 | Form: LOTION
Manufacturer: Byoma Ltd
Category: otc | Type: HUMAN OTC DRUG LABEL
Date: 20250423

ACTIVE INGREDIENTS: SALICYLIC ACID 20 mg/1 mL
INACTIVE INGREDIENTS: PHYTOSPHINGOSINE; GLYCERYL STEARATE SE; RUTIN; ETHYL LINOLEATE; PHENOXYETHANOL; CAPRYLIC/CAPRIC TRIGLYCERIDE; SOYBEAN OIL; HYDROXYCINNAMIC ACID; SODIUM HYDROXIDE; HAMAMELIS VIRGINIANA TOP WATER; TOCOPHEROL; AMMONIUM POLYACRYLOYLDIMETHYL TAURATE; WATER; CERAMIDE NP; ETHYLHEXYLGLYCERIN; BAKUCHIOL; GLYCERIN; CETEARYL ALCOHOL; PROPANEDIOL; SAFFLOWER OIL

Byoma Acne Control Body Lotion

Active ingredient

Salicylic Acid 2%

Purpose

Acne Treatment

Use

- for the treatment of acne

Warnings

For external use only

When using this product

- skin irritation and dryness is more likely to occur if you use another topical acne medication at the same time. If irritation occurs, only use one topical acne medication at a time.

Stop use and ask a doctor if

- skin irritation occurs or gets worse.

Keep out of reach of children.

If swallowed, get medical help or contact a Poison Control Centre right away.

Directions

- clean the skin thoroughly before applying this product
- cover the entire affected area with a thin layer one to three times daily
- because excessive drying of the skin may occur, start with one application daily, then gradually increase to two or three times daily if needed or as directed by a doctor
- if bothersome dryness or peeling occurs, reduce application to once a day or every other day.

Other Information

Protect the product in this container from excessive heat and direct sun.

Inactive Ingredients

Aqua (Water), Cetearyl Alcohol, Caprylic/Capric Triglyceride, Glycerin, Hamamelis Virginiana (Witch Hazel) Water, Glyceryl Stearate SE, Ammonium Polyacryloyldimethyl Taurate, Glycine Soja (Soybean) Oil, Ethyl Linoleate, Carthamus Tinctorius (Safflower) Seed Oil, Phenoxyethanol, Sodium Hydroxide, Phytosphingosine, Ceramide NP, Ethylhexylglycerin, Bakuchiol, Tocopherol, Rutin, Hydroxycinnamic Acid, Propanediol

Questions or Comments?

Contact hello@byoma.com